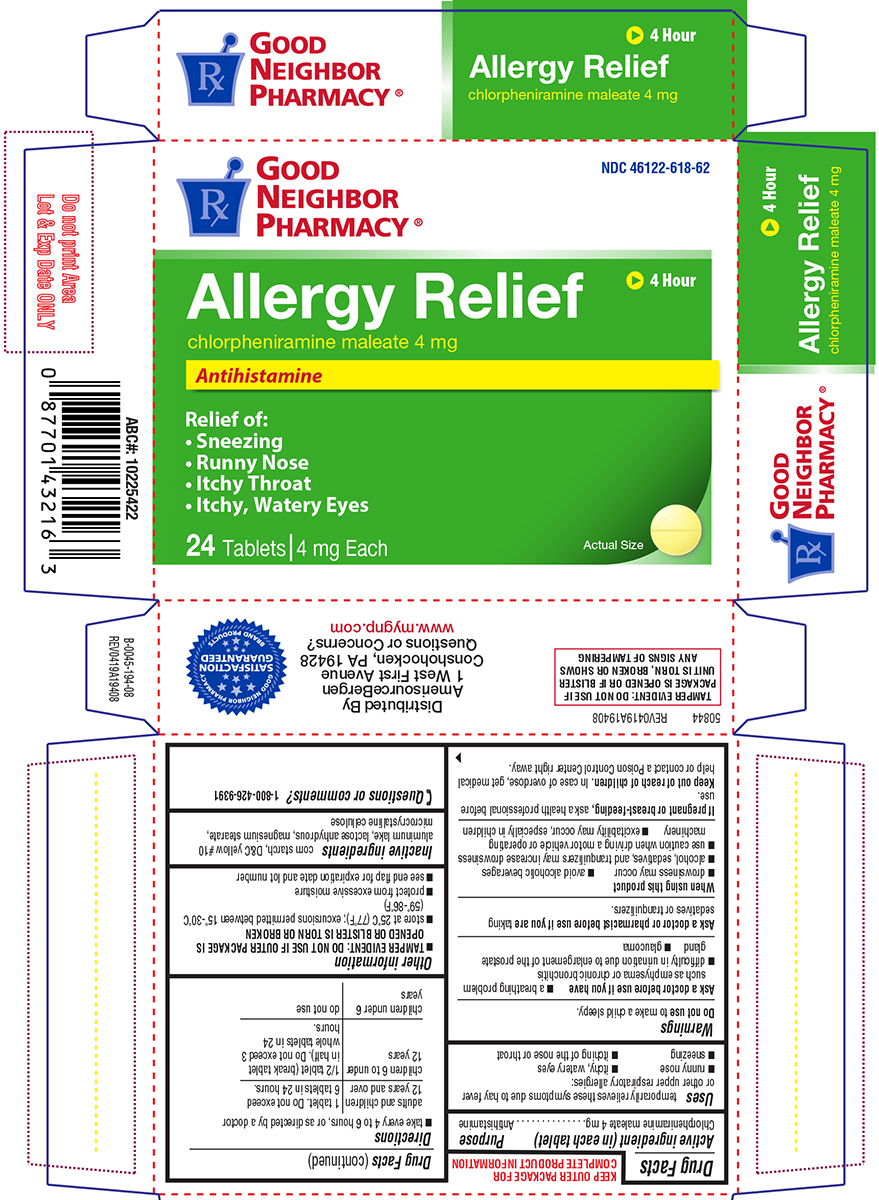 DRUG LABEL: Allergy Relief
NDC: 46122-618 | Form: TABLET
Manufacturer: Amerisource Bergen
Category: otc | Type: HUMAN OTC DRUG LABEL
Date: 20260218

ACTIVE INGREDIENTS: CHLORPHENIRAMINE MALEATE 4 mg/1 1
INACTIVE INGREDIENTS: STARCH, CORN; D&C YELLOW NO. 10 ALUMINUM LAKE; ANHYDROUS LACTOSE; MAGNESIUM STEARATE; MICROCRYSTALLINE CELLULOSE

Good Neighbor Pharmacy 44-194

Active ingredient (in each tablet)

Chlorpheniramine maleate 4 mg

Purpose

Antihistamine

Uses

temporarily relieves these symptoms due to hay fever or other upper respiratory allergies:

- runny nose
- itchy, watery eyes
- sneezing
- itching of the nose or throat

Warnings

Do not use

to make a child sleepy.

Ask a doctor before use if you have

- glaucoma
- a breathing problem such as emphysema or chronic bronchitis
- difficulty in urination due to enlargement of the prostate gland

Ask a doctor or pharmacist before use if you are

taking sedatives or tranquilizers.

When using this product

- drowsiness may occur
- avoid alcoholic beverages
- alcohol, sedatives, and tranquilizers may increase drowsiness
- use caution when driving a motor vehicle or operating machinery
- excitability may occur, especially in children

If pregnant or breast-feeding,

ask a health professional before use.

Keep out of reach of children.

In case of overdose, get medical help or contact a Poison Control Center right away.

Directions

- take every 4 to 6 hours, or as directed by a doctor

adults and children 12 years and over | 1 tablet. Do not exceed 6 tablets in 24 hours.
children 6 to under 12 years | 1/2 tablet (break tablet in half). Do not exceed 3 whole tablets in 24 hours.
children under 6 years | do not use

Other information

- TAMPER EVIDENT: DO NOT USE IF OUTER PACKAGE IS OPENED OR BLISTER IS TORN OR BROKEN
- store at 25ºC (77ºF); excursions permitted between 15º-30ºC (59º-86ºF)
- protect from excessive moisture
- see end flap for expiration date and lot number

Inactive ingredients

corn starch, D&C yellow #10 aluminum lake, lactose anhydrous, magnesium stearate, microcrystalline cellulose

Questions or comments?

1-800-426-9391

Principal Display Panel

Good
Neighbor
Pharmacy®

NDC 46122-618-62

Allergy Relief
chlorpheniramine maleate 4 mg

Antihistamine

4 Hour

Relief of:
• Sneezing
• Runny Nose
• Itchy Throat
• Itchy, Watery Eyes

24 Tablets | 4 mg Each

Actual Size

TAMPER EVIDENT: DO NOT USE IF PACKAGE IS
OPENED OR IF BLISTER UNIT IS TORN, BROKEN OR
SHOWS ANY SIGNS OF TAMPERING

50844 REV0419A19408

Distributed By
AmerisourceBergen
1 West First Avenue
Conshohocken, PA 19428
Questions or Concerns?
www.mygnp.com

GNP 44-194